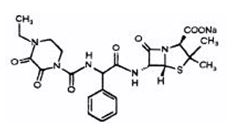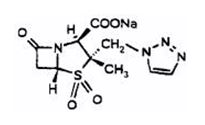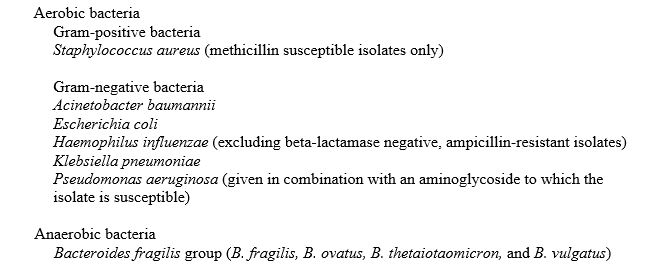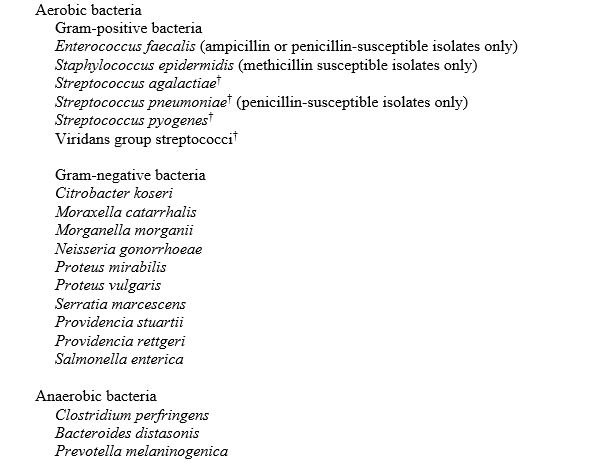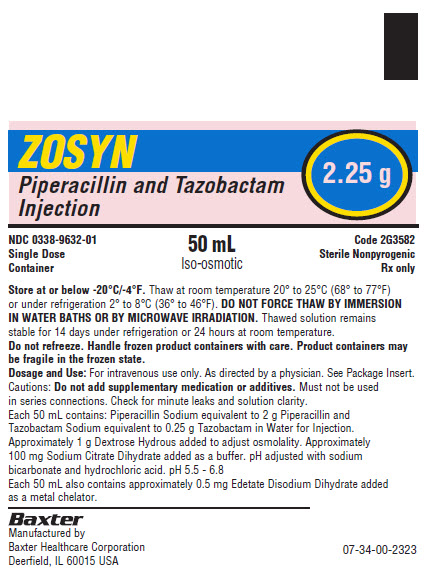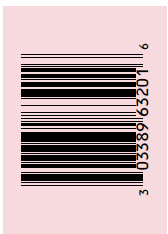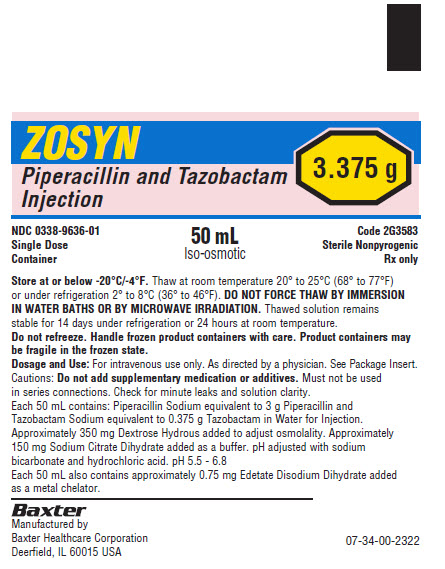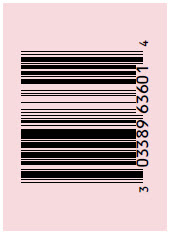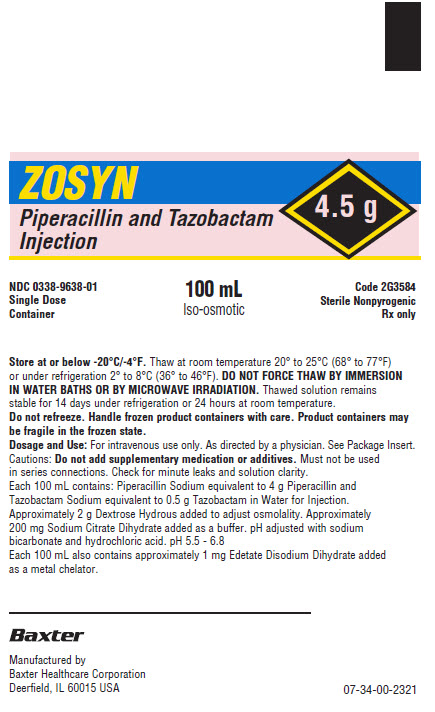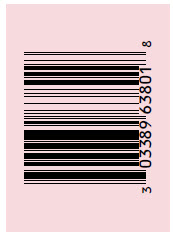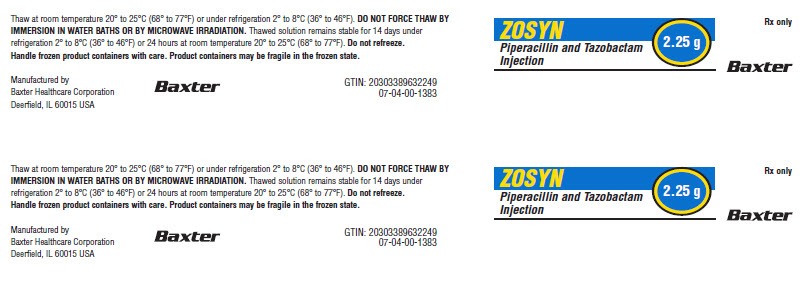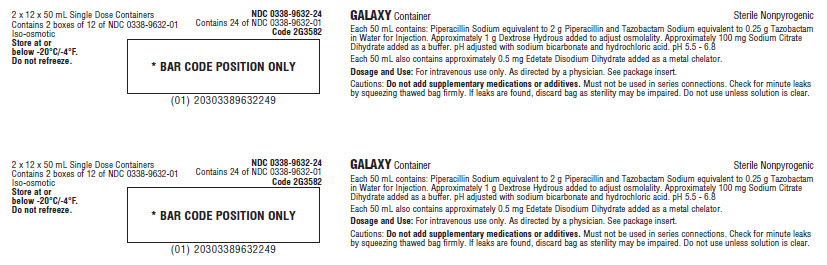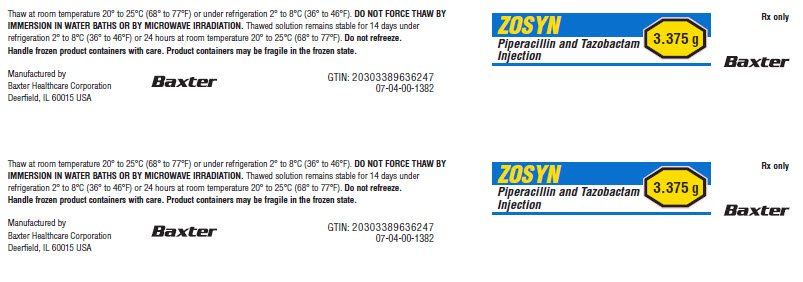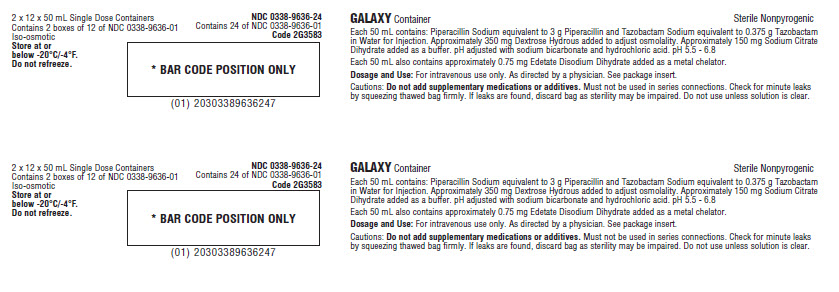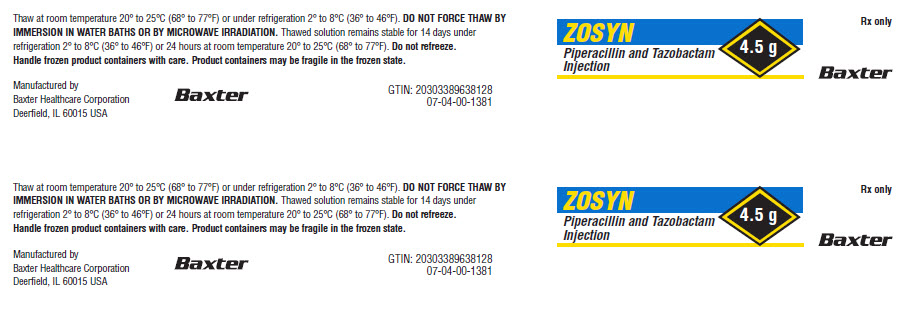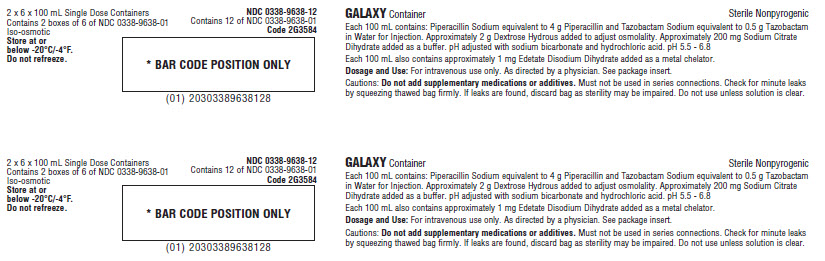 DRUG LABEL: Zosyn
NDC: 0338-9632 | Form: INJECTION, SOLUTION
Manufacturer: Baxter Healthcare Corporation
Category: prescription | Type: HUMAN PRESCRIPTION DRUG LABEL
Date: 20241203

ACTIVE INGREDIENTS: PIPERACILLIN SODIUM 2 g/50 mL; TAZOBACTAM SODIUM 0.25 g/50 mL
INACTIVE INGREDIENTS: DEXTROSE MONOHYDRATE 1 g/50 mL; SODIUM CITRATE, UNSPECIFIED FORM 100 mg/50 mL; EDETATE DISODIUM 0.5 mg/50 mL; SODIUM BICARBONATE; HYDROCHLORIC ACID; WATER

HIGHLIGHTS OF PRESCRIBING INFORMATION

These highlights do not include all the information needed to use ZOSYN safely and effectively. See full prescribing information for ZOSYN.
ZOSYN® (piperacillin and tazobactam) injection, for intravenous use
Initial U.S. Approval: 1993

RECENT MAJOR CHANGES

Warnings and Precautions, Rhabdomyolysis (5.4) MM/YYYY

1 INDICATIONS AND USAGE

ZOSYN is a combination of piperacillin, a penicillin‑class antibacterial and tazobactam, a beta‑lactamase inhibitor, indicated for the treatment of:

- Intra-abdominal infections in adult and pediatric patients 2 months of age and older (1.1)
- Nosocomial pneumonia in adult and pediatric patients 2 months of age and older (1.2)
- Skin and skin structure infections in adults (1.3)
- Female pelvic infections in adults (1.4)
- Community-acquired pneumonia in adults (1.5)

To reduce the development of drug-resistant bacteria and maintain the effectiveness of ZOSYN and other antibacterial drugs, ZOSYN should be used only to treat or prevent infections that are proven or strongly suspected to be caused by bacteria. (1.6)

2 DOSAGE AND ADMINISTRATION

- If a dose of ZOSYN is required that does not equal 2.25 g, 3.375 g, or 4.5 g, ZOSYN injection in GALAXY Containers is not recommended for use and an alternative formulation of ZOSYN should be considered. (2.1)
- Adult Patients With Indications Other Than Nosocomial Pneumonia; The usual daily dosage of ZOSYN for adults is 3.375 g every six hours totaling 13.5 g (12.0 g piperacillin and 1.5 g tazobactam). (2.2)
- Adult Patients with Nosocomial Pneumonia: Initial presumptive treatment of patients with nosocomial pneumonia should start with ZOSYN at a dosage of 4.5 g every six hours plus an aminoglycoside, totaling 18.0 g (16.0 g piperacillin and 2.0 g tazobactam). (2.3)
- Adult Patients with Renal Impairment: Dosage in patients with renal impairment (creatinine clearance ≤40 mL/min) and dialysis patients should be reduced, based on the degree of renal impairment. (2.4)
- Pediatric Patients by Indication and Age: See Table below (2.5)

Recommended Dosage of ZOSYN for Pediatric Patients 2 months of Age and Older, Weighing up to 40 Kg and With Normal Renal Function
Age | Appendicitis and /or Peritonitis | Nosocomial Pneumonia
2 months to 9 months | 90 mg/kg (80 mg piperacillin and 10 mg tazobactam) every 8 (eight) hours | 90 mg/kg (80 mg piperacillin and 10 mg tazobactam) every 6 (six) hours
Older than 9 months | 112.5 mg/kg (100 mg piperacillin and 12.5 mg tazobactam) every 8 (eight) hours | 112.5 mg/kg (100 mg piperacillin and 12.5 mg tazobactam) every 6 (six) hours

- Administer ZOSYN by intravenous infusion over 30 minutes to both adult and pediatric patients (2.2, 2.3, 2.4, 2.5).
- ZOSYN and aminoglycosides should be reconstituted, diluted, and administered separately. Co-administration via Y-site can be done under certain conditions. (2.7)
- See the full prescribing information for the preparation and administration instructions for ZOSYN Injection in GALAXY Containers.

3 DOSAGE FORMS AND STRENGTHS

ZOSYN® Injection: 2.25 g in 50 mL, 3.375 g in 50 mL, and 4.5 g in 100 mL frozen solution in single-dose GALAXY Containers. (3, 16)

4 CONTRAINDICATIONS

Patients with a history of allergic reactions to any of the penicillins, cephalosporins, or beta-lactamase inhibitors. (4)

5 WARNINGS AND PRECAUTIONS

- Serious hypersensitivity reactions (anaphylactic/anaphylactoid) reactions have been reported in patients receiving ZOSYN. Discontinue ZOSYN if a reaction occurs. (5.1)
- ZOSYN may cause severe cutaneous adverse reactions, such as Stevens‑Johnson syndrome, toxic epidermal necrolysis, drug reaction with eosinophilia and systemic symptoms, and acute generalized exanthematous pustulosis. Discontinue ZOSYN for progressive rashes. (5.2)
- Hemophagocytic lymphohistiocytosis (HLH) has been reported with the use of ZOSYN. If HLH is suspected, discontinue ZOSYN immediately. (5.3)
- Rhabdomyolysis: If signs or symptoms of rhabdomyolysis are observed, discontinue ZOSYN and initiate appropriate therapy. (5.4)
- Hematological effects (including bleeding, leukopenia and neutropenia) have occurred. Monitor hematologic tests during prolonged therapy. (5.5)
- As with other penicillins, ZOSYN may cause neuromuscular excitability or seizures. Patients receiving higher doses, especially in the presence of renal impairment may be at greater risk. Closely monitor patients with renal impairment or seizure disorders for signs and symptoms of neuromuscular excitability or seizures. (5.6)
- Nephrotoxicity in critically ill patients has been observed; the use of ZOSYN was found to be an independent risk factor for renal failure and was associated with delayed recovery of renal function as compared to other beta-lactam antibacterial drugs in a randomized, multicenter, controlled trial in critically ill patients. Based on this study, alternative treatment options should be considered in the critically ill population. If alternative treatment options are inadequate or unavailable, monitor renal function during treatment with ZOSYN. (5.7)
- Clostridioides difficile-associated diarrhea: evaluate patients if diarrhea occurs. (5.9)

6 ADVERSE REACTIONS

The most common adverse reactions (incidence >5%) are diarrhea, constipation, nausea, headache, and insomnia. (6.1)

To report SUSPECTED ADVERSE REACTIONS, contact Baxter Healthcare at 1-866-888-2472 or FDA at 1-800-FDA-1088 or www.fda.gov/medwatch.

7 DRUG INTERACTIONS

- ZOSYN administration can significantly reduce tobramycin concentrations in hemodialysis patients. Monitor tobramycin concentrations in these patients. (7.1)
- Probenecid prolongs the half-lives of piperacillin and tazobactam and should not be co-administered with ZOSYN unless the benefit outweighs the risk. (7.2)
- Co-administration of ZOSYN with vancomycin may increase the incidence of acute kidney injury. Monitor kidney function in patients receiving ZOSYN and vancomycin. (7.3)
- Monitor coagulation parameters in patients receiving ZOSYN and heparin or oral anticoagulants. (7.4)
- ZOSYN may prolong the neuromuscular blockade of vecuronium and other non-depolarizing neuromuscular blockers. Monitor for adverse reactions related to neuromuscular blockade. (7.5)

8 USE IN SPECIFIC POPULATIONS

Dosage in patients with renal impairment (creatinine clearance ≤40 mL/min) should be reduced based on the degree of renal impairment. (2.4, 8.6)

FULL PRESCRIBING INFORMATION

1 INDICATIONS AND USAGE

1.1 Intra-abdominal Infections

ZOSYN is indicated in adults and pediatric patients (2 months of age and older) for the treatment of appendicitis (complicated by rupture or abscess) and peritonitis caused by beta-lactamase producing isolates of Escherichia coli or the following members of the Bacteroides fragilis group: B. fragilis, B. ovatus, B. thetaiotaomicron, or B. vulgatus.

1.2 Nosocomial Pneumonia

ZOSYN is indicated in adults and pediatric patients (2 months of age and older) for the treatment of nosocomial pneumonia (moderate to severe) caused by beta-lactamase producing isolates of Staphylococcus aureus and by piperacillin and tazobactam-susceptible Acinetobacter baumannii, Haemophilus influenzae, Klebsiella pneumoniae, and Pseudomonas aeruginosa (Nosocomial pneumonia caused by P. aeruginosa should be treated in combination with an aminoglycoside) [see Dosage and Administration (2)].

1.3 Skin and Skin Structure Infections

ZOSYN is indicated in adults for the treatment of uncomplicated and complicated skin and skin structure infections, including cellulitis, cutaneous abscesses and ischemic/diabetic foot infections caused by beta-lactamase producing isolates of Staphylococcus aureus.

1.4 Female Pelvic Infections

ZOSYN is indicated in adults for the treatment of postpartum endometritis or pelvic inflammatory disease caused by beta-lactamase producing isolates of Escherichia coli.

1.5 Community-acquired Pneumonia

ZOSYN is indicated in adults for the treatment of community-acquired pneumonia (moderate severity only) caused by beta-lactamase producing isolates of Haemophilus influenzae.

1.6 Usage

To reduce the development of drug-resistant bacteria and maintain the effectiveness of ZOSYN and other antibacterial drugs, ZOSYN should be used only to treat or prevent infections that are proven or strongly suspected to be caused by bacteria. When culture and susceptibility information are available, they should be considered in selecting or modifying antibacterial therapy. In the absence of such data, local epidemiology and susceptibility patterns may contribute to the empiric selection of therapy.

2 DOSAGE AND ADMINISTRATION

2.1 Important Administration Instructions

If a dose of ZOSYN is required that does not equal 2.25 g, 3.375 g, or 4.5 g, ZOSYN injection in GALAXY Containers is not recommended for use and an alternative formulation of ZOSYN should be considered.

2.2 Dosage in Adult Patients With Indications Other Than Nosocomial Pneumonia

The usual total daily dosage of ZOSYN for adult patients with indications other than nosocomial pneumonia is 3.375 g every six hours [totaling 13.5 g (12.0 g piperacillin and 1.5 g tazobactam)], to be administered by intravenous infusion over 30 minutes. The usual duration of ZOSYN treatment is from 7 to 10 days.

2.3 Dosage in Adult Patients With Nosocomial Pneumonia

Initial presumptive treatment of adult patients with nosocomial pneumonia should start with ZOSYN at a dosage of 4.5 g every six hours plus an aminoglycoside, [totaling 18.0 g (16.0 g piperacillin and 2.0 g tazobactam)], administered by intravenous infusion over 30 minutes. The recommended duration of ZOSYN treatment for nosocomial pneumonia is 7 to 14 days. Treatment with the aminoglycoside should be continued in patients from whom P. aeruginosa is isolated.

2.4 Dosage in Adult Patients With Renal Impairment

In adult patients with renal impairment (creatinine clearance ≤ 40 mL/min) and dialysis patients (hemodialysis and CAPD), the intravenous dose of ZOSYN should be reduced based on the degree of renal impairment. The recommended daily dosage of ZOSYN for patients with renal impairment administered by intravenous infusion over 30 minutes is described in Table 1.

Table 1: Recommended Dosage of ZOSYN in Patients with Normal Renal Function and Renal Impairment (As total grams piperacillin and tazobactam) [Administer ZOSYN by intravenous infusion over 30 minutes.]
Creatinine clearance, mL/min | All Indications (except nosocomial pneumonia) | Nosocomial Pneumonia
Greater than 40 mL/min | 3.375 every 6 hours | 4.5 every 6 hours
20 to 40 mL/min [Creatinine clearance for patients not receiving hemodialysis] | 2.25 every 6 hours | 3.375 every 6 hours
Less than 20 mL/min | 2.25 every 8 hours | 2.25 every 6 hours
Hemodialysis [0.75 g (0.67 g piperacillin and 0.08 g tazobactam) should be administered following each hemodialysis session on hemodialysis days] | 2.25 every 12 hours | 2.25 every 8 hours
CAPD | 2.25 every 12 hours | 2.25 every 8 hours

For patients on hemodialysis, the maximum dose is 2.25 g every twelve hours for all indications other than nosocomial pneumonia and 2.25 g every eight hours for nosocomial pneumonia. Since hemodialysis removes 30% to 40% of the administered dose, an additional dose of 0.75 g ZOSYN (0.67 g piperacillin and 0.08 g tazobactam) should be administered following each dialysis period on hemodialysis days. No additional dosage of ZOSYN is necessary for CAPD patients.

2.5 Dosage in Pediatric Patients With Appendicitis/Peritonitis or Nosocomial Pneumonia

The recommended dosage for pediatric patients with appendicitis and/or peritonitis or nosocomial pneumonia aged 2 months of age and older, weighing up to 40 kg, and with normal renal function, is described in Table 2 [see Use in Specific Populations (8.4) and Clinical Pharmacology (12.3)].

Table 2: Recommended Dosage of ZOSYN in Pediatric Patients 2 Months of Age and Older, Weighing Up to 40 kg, and With Normal Renal Function [Administer ZOSYN by intravenous infusion over 30 minutes] [If a dose of ZOSYN is required that does not equal 2.25 g, 3.375 g, or 4.5 g, ZOSYN injection in GALAXY Containers is not recommended for use and an alternative formulation of ZOSYN should be considered [see Use in Specific Populations (8.4)].]
Age | Appendicitis and/or Peritonitis | Nosocomial Pneumonia
2 months to 9 months | 90 mg/kg; (80 mg piperacillin and 10 mg tazobactam) every 8 (eight) hours | 90 mg/kg; (80 mg piperacillin and 10 mg tazobactam); every 6 (six) hours
Older than 9 months of age | 112.5 mg/kg; (100 mg piperacillin and 12.5 mg tazobactam); every 8 (eight) hours | 112.5 mg/kg; (100 mg piperacillin and 12.5 mg tazobactam); every 6 (six) hours

Pediatric patients weighing over 40 kg and with normal renal function should receive the adult dose [see Dosage and Administration (2.2, 2.3)].

Dosage of ZOSYN in pediatric patients with renal impairment has not been determined.

2.6 Directions for Use of ZOSYN Injection

Important Administration Instructions for ZOSYN Injection in GALAXY Containers

Administer ZOSYN Injection in GALAXY Containers using sterile equipment, after thawing to room temperature.

ZOSYN containing EDTA is compatible for co-administration via a Y-site intravenous tube with Lactated Ringer’s injection, USP.

Unused portions of ZOSYN Injection should be discarded.

Do NOT use plastic containers in series connections. Such use could result in air embolism due to residual air being drawn from the primary container before administration of the fluid from the secondary container is complete.

Handle frozen product containers with care. Product containers may be fragile in the frozen state.

Thawing of Plastic Container

Thaw frozen container at room temperature 20°C to 25°C [68°F to 77°F] or under refrigeration (2°C to 8°C [36°F to 46°F]). Do not force thaw by immersion in water baths or by microwave irradiation.

Check for minute leaks by squeezing container firmly. If leaks are detected, discard solution as sterility may be impaired.

The container should be visually inspected. Components of the solution may precipitate in the frozen state and will dissolve upon reaching room temperature with little or no agitation. Potency is not affected. Agitate after solution has reached room temperature. If after visual inspection, the solution remains cloudy or if an insoluble precipitate is noted or if any seals or outlet ports are not intact, the container should be discarded.

Administration Instructions for ZOSYN Injection in GALAXY Containers to Adult Patients

Administer by infusion over a period of at least 30 minutes. During the infusion it is desirable to discontinue the primary infusion solution.

Administration Instruction for ZOSYN Injection in GALAXY Containers to Pediatric Patients Weighing up to 40 kg

If a dose of ZOSYN is required that does not equal 2.25 g, 3.375 g, or 4.5 g, ZOSYN injection in GALAXY Containers is not recommended for use and an alternative formulation of ZOSYN should be considered.

Storage of ZOSYN Injection

Store in a freezer capable of maintaining a temperature of -20°C (-4°F).

For GALAXY Containers, the thawed solution is stable for 14 days under refrigeration (2°C to 8°C [36°F to 46°F]) or 24 hours at room temperature 20°C to 25°C [68°F to 77°F]. Do not refreeze thawed ZOSYN Injection.

2.7 Compatibility With Aminoglycosides

Due to the in vitro inactivation of aminoglycosides by piperacillin, ZOSYN and aminoglycosides are recommended for separate administration. ZOSYN and aminoglycosides should be reconstituted, diluted, and administered separately when concomitant therapy with aminoglycosides is indicated [see Drug Interactions (7.1)].

In circumstances where co-administration via Y-site is necessary, ZOSYN formulations containing EDTA are compatible for simultaneous co-administration via Y-site infusion only with the following aminoglycosides under the following conditions:

Table 3: Compatibility with Aminoglycosides
Aminoglycoside | ZOSYN Dose; (grams) | Aminoglycoside; Concentration; Range [The concentration ranges in Table 3 are based on administration of the aminoglycoside in divided doses (10-15 mg/kg/day in two daily doses for amikacin and 3-5 mg/kg/day in three daily doses for gentamicin). Administration of amikacin or gentamicin in a single daily dose or in doses exceeding those stated above via Y-site with ZOSYN containing EDTA has not been evaluated. See package insert for each aminoglycoside for complete Dosage and Administration instructions.]; (mg/mL) | Acceptable Diluents
Amikacin | 2.25; 3.375; 4.5 | 1.75 - 7.5 | 0.9% sodium chloride or 5% dextrose
Gentamicin | 2.25; 3.375 [ZOSYN 3.375 g per 50 mL GALAXY Containers are NOT compatible with gentamicin for co-administration via a Y-site due to the higher concentrations of piperacillin and tazobactam.]; 4.5 | 0.7 - 3.32 | 0.9% sodium chloride or 5% dextrose

Only the concentration and diluents for amikacin or gentamicin with the dosages of ZOSYN listed above have been established as compatible for co-administration via Y-site infusion. Simultaneous co-administration via Y-site infusion in any manner other than listed above may result in inactivation of the aminoglycoside by ZOSYN.

ZOSYN is not compatible with tobramycin for simultaneous co-administration via Y-site infusion. Compatibility of ZOSYN with other aminoglycosides has not been established.

Parenteral drug products should be inspected visually for particulate matter and discoloration prior to administration, whenever solution and container permit.

3 DOSAGE FORMS AND STRENGTHS

ZOSYN® (piperacillin and tazobactam) Injection is supplied in GALAXY Containers as a frozen, iso-osmotic, sterile, non-pyrogenic solution in single-dose plastic containers:

2.25 g (piperacillin sodium equivalent to 2 g piperacillin and tazobactam sodium equivalent to 0.25 g tazobactam) in 50 mL.

3.375 g (piperacillin sodium equivalent to 3 g piperacillin and tazobactam sodium equivalent to 0.375 g tazobactam) in 50 mL.

4.5 g (piperacillin sodium equivalent to 4 g piperacillin and tazobactam sodium equivalent to 0.5 g tazobactam) in 100 mL.

4 CONTRAINDICATIONS

ZOSYN is contraindicated in patients with a history of allergic reactions to any of the penicillins, cephalosporins, or beta-lactamase inhibitors.

5 WARNINGS AND PRECAUTIONS

5.1 Hypersensitivity Adverse Reactions

Serious and occasionally fatal hypersensitivity (anaphylactic/anaphylactoid) reactions (including shock) have been reported in patients receiving therapy with ZOSYN. These reactions are more likely to occur in individuals with a history of penicillin, cephalosporin, or carbapenem hypersensitivity or a history of sensitivity to multiple allergens. Before initiating therapy with ZOSYN, careful inquiry should be made concerning previous hypersensitivity reactions. If an allergic reaction occurs, ZOSYN should be discontinued and appropriate therapy instituted.

5.2 Severe Cutaneous Adverse Reactions

ZOSYN may cause severe cutaneous adverse reactions, such as Stevens-Johnson syndrome, toxic epidermal necrolysis, drug reaction with eosinophilia and systemic symptoms, and acute generalized exanthematous pustulosis. If patients develop a skin rash they should be monitored closely and ZOSYN discontinued if lesions progress.

5.3 Hemophagocytic Lymphohistiocytosis

Cases of hemophagocytic lymphohistiocytosis (HLH) have been reported in pediatric and adult patients treated with ZOSYN. Signs and symptoms of HLH may include fever, rash, lymphadenopathy, hepatosplenomegaly and cytopenia. If HLH is suspected, discontinue ZOSYN immediately and institute appropriate management.

5.4 Rhabdomyolysis

Rhabdomyolysis has been reported with the use of piperacillin and tazobactam [see Adverse Reactions (6.2)]. If signs or symptoms of rhabdomyolysis such as muscle pain, tenderness or weakness, dark urine, or elevated creatine phosphokinase are observed, discontinue ZOSYN and initiate appropriate therapy.

5.5 Hematologic Adverse Reactions

Bleeding manifestations have occurred in some patients receiving beta-lactam drugs, including piperacillin. These reactions have sometimes been associated with abnormalities of coagulation tests such as clotting time, platelet aggregation and prothrombin time, and are more likely to occur in patients with renal failure. If bleeding manifestations occur, ZOSYN should be discontinued and appropriate therapy instituted.

The leukopenia/neutropenia associated with ZOSYN administration appears to be reversible and most frequently associated with prolonged administration.

Periodic assessment of hematopoietic function should be performed, especially with prolonged therapy, i.e., ≥ 21 days [see Adverse Reactions (6.1)].

5.6 Central Nervous System Adverse Reactions

As with other penicillins, ZOSYN may cause neuromuscular excitability or seizures. Patients receiving higher doses, especially patients with renal impairment may be at greater risk for central nervous system adverse reactions. Closely monitor patients with renal impairment or seizure disorders for signs and symptoms of neuromuscular excitability or seizures [see Adverse Reactions (6.2)].

5.7 Nephrotoxicity in Critically Ill Patients

The use of ZOSYN was found to be an independent risk factor for renal failure and was associated with delayed recovery of renal function as compared to other beta-lactam antibacterial drugs in a randomized, multicenter, controlled trial in critically ill patients [see Adverse Reactions (6.1)]. Based on this study, alternative treatment options should be considered in the critically ill population. If alternative treatment options are inadequate or unavailable, monitor renal function during treatment with ZOSYN [see Dosage and Administration (2.4)].

Combined use of piperacillin and tazobactam and vancomycin may be associated with an increased incidence of acute kidney injury [see Drug Interactions (7.3)].

5.8 Electrolyte Effects

ZOSYN contains a total of 2.84 mEq (65 mg) of Na^+ (sodium) per gram of piperacillin in the combination product. This should be considered when treating patients requiring restricted salt intake. Periodic electrolyte determinations should be performed in patients with low potassium reserves, and the possibility of hypokalemia should be kept in mind with patients who have potentially low potassium reserves and who are receiving cytotoxic therapy or diuretics.

5.9 Clostridioides difficile-Associated Diarrhea

Clostridioides difficile-associated diarrhea (CDAD) has been reported with use of nearly all antibacterial agents, including ZOSYN, and may range in severity from mild diarrhea to fatal colitis. Treatment with antibacterial agents alters the normal flora of the colon leading to overgrowth of C. difficile.

C. difficile produces toxins A and B which contribute to the development of CDAD. Hypertoxin producing strains of C. difficile cause increased morbidity and mortality, as these infections can be refractory to antimicrobial therapy and may require colectomy. CDAD must be considered in all patients who present with diarrhea following antibacterial drug use. Careful medical history is necessary since CDAD has been reported to occur over two months after the administration of antibacterial agents.

If CDAD is suspected or confirmed, ongoing antibacterial drug use not directed against C. difficile may need to be discontinued. Appropriate fluid and electrolyte management, protein supplementation, antibacterial treatment of C. difficile, and surgical evaluation should be instituted as clinically indicated.

5.10 Development of Drug-Resistant Bacteria

Prescribing ZOSYN in the absence of a proven or strongly suspected bacterial infection or a prophylactic indication is unlikely to provide benefit to the patient and increases the risk of development of drug-resistant bacteria.

6 ADVERSE REACTIONS

The following clinically significant adverse reactions are described elsewhere in the labeling:

- Hypersensitivity Adverse Reactions [see Warnings and Precautions (5.1)]
- Severe Cutaneous Adverse Reactions [see Warnings and Precautions (5.2)]
- Hemophagocytic Lymphohistiocytosis [see Warnings and Precautions (5.3)]
- Rhabdomyolysis [see Warnings and Precautions (5.4)]
- Hematologic Adverse Reactions [see Warnings and Precautions (5.5)]
- Central Nervous System Adverse Reactions [see Warnings and Precautions (5.6)]
- Nephrotoxicity in Critically Ill Patients [see Warnings and Precautions (5.7)]
- Clostridioides difficile-Associated Diarrhea [see Warnings and Precautions (5.9)]

6.1 Clinical Trials Experience

Because clinical trials are conducted under widely varying conditions, adverse reaction rates observed in the clinical trials of a drug cannot be directly compared to rates in the clinical trials of another drug and may not reflect the rates observed in practice.

Clinical Trials in Adult Patients

During the initial clinical investigations, 2621 patients worldwide were treated with ZOSYN in phase 3 trials. In the key North American monotherapy clinical trials (n=830 patients), 90% of the adverse events reported were mild to moderate in severity and transient in nature. However, in 3.2% of the patients treated worldwide, ZOSYN was discontinued because of adverse events primarily involving the skin (1.3%), including rash and pruritus; the gastrointestinal system (0.9%), including diarrhea, nausea, and vomiting; and allergic reactions (0.5%).

Table 4: Adverse Reactions from ZOSYN Monotherapy Clinical Trials

System Organ Class

Adverse Reaction

Gastrointestinal disorders

Diarrhea (11.3%)
Constipation (7.7%)
Nausea (6.9%)
Vomiting (3.3%)
Dyspepsia (3.3%)
Abdominal pain (1.3%)

General disorders and administration site conditions

Fever (2.4%)
Injection site reaction (≤1%)
Rigors (≤1%)

Immune system disorders

Anaphylaxis (≤1%)

Infections and infestations

Candidiasis (1.6%)
Pseudomembranous colitis (≤1%)

Metabolism and nutrition disorders

Hypoglycemia (≤1%)

Musculoskeletal and connective tissue disorders

Myalgia (≤1%)
Arthralgia (≤1%)

Nervous system disorders

Headache (7.7%)

Psychiatric disorders

Insomnia (6.6%)

Skin and subcutaneous tissue disorders

Rash (4.2%, including maculopapular, bullous, and urticarial)
Pruritus (3.1%)
Purpura (≤1%)

Vascular disorders

Phlebitis (1.3%)
Thrombophlebitis (≤1%)
Hypotension (≤1%)
Flushing (≤1%)

Respiratory, thoracic and mediastinal disorders

Epistaxis (≤1%)

Nosocomial Pneumonia Trials

Two trials of nosocomial lower respiratory tract infections were conducted. In one study, 222 patients were treated with ZOSYN in a dosing regimen of 4.5 g every 6 hours in combination with an aminoglycoside and 215 patients were treated with imipenem/cilastatin (500 mg/500 mg every 6 hours) in combination with an aminoglycoside. In this trial, treatment-emergent adverse events were reported by 402 patients, 204 (91.9%) in the piperacillin and tazobactam group and 198 (92.1%) in the imipenem/cilastatin group. Twenty-five (11.0%) patients in the piperacillin and tazobactam group and 14 (6.5%) in the imipenem/cilastatin group (p > 0.05) discontinued treatment due to an adverse event.

The second trial used a dosing regimen of 3.375 g given every 4 hours with an aminoglycoside.

Table 5: Adverse Reactions from ZOSYN Plus Aminoglycoside Clinical Trials [For adverse drug reactions that appeared in both studies the higher frequency is presented.]

System Organ Class

Adverse Reaction

Blood and lymphatic system disorders

Thrombocythemia (1.4%)
Anemia (≤1%)
Thrombocytopenia (≤1%)
Eosinophilia (≤1%)

Gastrointestinal disorders

Diarrhea (20%)
Constipation (8.4%)
Nausea (5.8%)
Vomiting (2.7%)
Dyspepsia (1.9%)
Abdominal pain (1.8%)
Stomatitis (≤1%)

General disorders and administration site conditions

Fever (3.2%)
Injection site reaction (≤1%)

Infections and infestations

Oral candidiasis (3.9%)
Candidiasis (1.8%)

Investigations

BUN increased (1.8%)
Blood creatinine increased (1.8%)
Liver function test abnormal (1.4%)
Alkaline phosphatase increased (≤1%)
Aspartate aminotransferase increased (≤1%)
Alanine aminotransferase increased (≤1%)

Metabolism and nutrition disorders

Hypoglycemia (≤1%)
Hypokalemia (≤1%)

Nervous system disorders

Headache (4.5%)

Psychiatric disorders

Insomnia (4.5%)

Renal and urinary disorders

Renal failure (≤1%)

Skin and subcutaneous tissue disorders

Rash (3.9%)
Pruritus (3.2%)

Vascular disorders

Thrombophlebitis (1.3%)
Hypotension (1.3%)

Other Trials: Nephrotoxicity

In a randomized, multicenter, controlled trial in 1200 adult critically ill patients, piperacillin and tazobactam was found to be a risk factor for renal failure (odds ratio 1.7, 95% CI 1.18 to 2.43), and associated with delayed recovery of renal function as compared to other beta‑lactam antibacterial drugs^1 [see Warnings and Precautions (5.7)].

Adverse Laboratory Changes (Seen During Clinical Trials)

Of the trials reported, including that of nosocomial lower respiratory tract infections in which a higher dose of ZOSYN was used in combination with an aminoglycoside, changes in laboratory parameters include:

Hematologic—decreases in hemoglobin and hematocrit, thrombocytopenia, increases in platelet count, eosinophilia, leukopenia, neutropenia. These patients were withdrawn from therapy; some had accompanying systemic symptoms (e.g., fever, rigors, chills)

Coagulation—positive direct Coombs' test, prolonged prothrombin time, prolonged partial thromboplastin time

Hepatic—transient elevations of AST (SGOT), ALT (SGPT), alkaline phosphatase, bilirubin

Renal—increases in serum creatinine, blood urea nitrogen

Additional laboratory events include abnormalities in electrolytes (i.e., increases and decreases in sodium, potassium, and calcium), hyperglycemia, decreases in total protein or albumin, blood glucose decreased, gamma-glutamyltransferase increased, hypokalemia, and bleeding time prolonged.

Clinical Trials in Pediatric Patients

Clinical studies of ZOSYN in pediatric patients suggest a similar safety profile to that seen in adults.

In a prospective, randomized, comparative, open-label clinical trial of pediatric patients, 2 to 12 years of age, with intra-abdominal infections (including appendicitis and/or peritonitis), 273 patients were treated with ZOSYN 112.5 mg/kg given IV every 8 hours and 269 patients were treated with cefotaxime (50 mg/kg) plus metronidazole (7.5 mg/kg) every 8 hours. In this trial, treatment-emergent adverse events were reported by 146 patients, 73 (26.7%) in the ZOSYN group and 73 (27.1%) in the cefotaxime/metronidazole group. Six patients (2.2%) in the ZOSYN group and 5 patients (1.9%) in the cefotaxime/metronidazole group discontinued due to an adverse event.

In a retrospective, cohort study, 140 pediatric patients 2 months to less than 18 years of age with nosocomial pneumonia were treated with ZOSYN and 267 patients were treated with comparators (which included ticarcillin-clavulanate, carbapenems, ceftazidime, cefepime, or ciprofloxacin). The rates of serious adverse reactions were generally similar between the ZOSYN and comparator groups, including patients aged 2 months to 9 months treated with ZOSYN 90 mg/kg IV every 6 hours and patients older than 9 months and less than 18 years of age treated with ZOSYN 112.5 mg/kg IV every 6 hours.

6.2 Postmarketing Experience

In addition to the adverse drug reactions identified in clinical trials in Table 4 and Table 5, the following adverse reactions have been identified during post-approval use of ZOSYN. Because these reactions are reported voluntarily from a population of uncertain size, it is not always possible to reliably estimate their frequency or establish a causal relationship to drug exposure.

Hepatobiliary—hepatitis, jaundice

Hematologic—hemolytic anemia, agranulocytosis, pancytopenia

Immune—hypersensitivity reactions, anaphylactic/anaphylactoid reactions (including shock), hemophagocytic lymphohistiocytosis (HLH), acute myocardial ischemia with or without myocardial infarction may occur as part of an allergic reaction.

Renal—interstitial nephritis

Nervous system disorders—seizures

Psychiatric disorders—delirium

Respiratory—eosinophilic pneumonia

Skin and Appendages—erythema multiforme, Stevens-Johnson syndrome, toxic epidermal necrolysis, drug reaction with eosinophilia and systemic symptoms, (DRESS), acute generalized exanthematous pustulosis (AGEP), dermatitis exfoliative, and linear IgA bullous dermatosis.

Musculoskeletal Disorders—rhabdomyolysis

Postmarketing experience with ZOSYN in pediatric patients suggests a similar safety profile to that seen in adults.

6.3 Additional Experience with Piperacillin

The following adverse reaction has also been reported for piperacillin for injection:

Skeletal—prolonged neuromuscular blockade [see Drug Interactions (7.5)].

7 DRUG INTERACTIONS

7.1 Aminoglycosides

Piperacillin may inactivate aminoglycosides by converting them to microbiologically inert amides.

In vivo inactivation:

When aminoglycosides are administered in conjunction with piperacillin to patients with end‑stage renal disease requiring hemodialysis, the concentrations of the aminoglycosides (especially tobramycin) may be significantly reduced and should be monitored.

Sequential administration of ZOSYN and tobramycin to patients with either normal renal function or mild to moderate renal impairment has been shown to modestly decrease serum concentrations of tobramycin but no dosage adjustment is considered necessary.

In vitro inactivation:

Due to the in vitro inactivation of aminoglycosides by piperacillin, ZOSYN and aminoglycosides are recommended for separate administration. ZOSYN and aminoglycosides should be reconstituted, diluted, and administered separately when concomitant therapy with aminoglycosides is indicated. ZOSYN, which contains EDTA, is compatible with amikacin and gentamicin for simultaneous Y-site infusion in certain diluents and at specific concentrations. ZOSYN is not compatible with tobramycin for simultaneous Y-site infusion [see Dosage and Administration (2.7)].

7.2 Probenecid

Probenecid administered concomitantly with ZOSYN prolongs the half-life of piperacillin by 21% and that of tazobactam by 71% because probenecid inhibits tubular renal secretion of both piperacillin and tazobactam. Probenecid should not be co-administered with ZOSYN unless the benefit outweighs the risk.

7.3 Vancomycin

Studies have detected an increased incidence of acute kidney injury in patients concomitantly administered piperacillin and tazobactam and vancomycin as compared to vancomycin alone [see Warnings and Precautions (5.7)].

Monitor kidney function in patients concomitantly administered with piperacillin and tazobactam and vancomycin.

No pharmacokinetic interactions have been noted between piperacillin and tazobactam and vancomycin.

7.4 Anticoagulants

Coagulation parameters should be tested more frequently and monitored regularly during simultaneous administration of high doses of heparin, oral anticoagulants, or other drugs that may affect the blood coagulation system or the thrombocyte function [see Warnings and Precautions (5.5)].

7.5 Vecuronium

Piperacillin when used concomitantly with vecuronium has been implicated in the prolongation of the neuromuscular blockade of vecuronium. ZOSYN could produce the same phenomenon if given along with vecuronium. Due to their similar mechanism of action, it is expected that the neuromuscular blockade produced by any of the non-depolarizing neuromuscular blockers could be prolonged in the presence of piperacillin. Monitor for adverse reactions related to neuromuscular blockade (see package insert for vecuronium bromide).

7.6 Methotrexate

Limited data suggests that co-administration of methotrexate and piperacillin may reduce the clearance of methotrexate due to competition for renal secretion. The impact of tazobactam on the elimination of methotrexate has not been evaluated. If concurrent therapy is necessary, serum concentrations of methotrexate as well as the signs and symptoms of methotrexate toxicity should be frequently monitored.

7.7 Effects on Laboratory Tests

There have been reports of positive test results using the Bio-Rad Laboratories Platelia Aspergillus EIA test in patients receiving piperacillin and tazobactam injection who were subsequently found to be free of Aspergillus infection. Cross-reactions with non‑Aspergillus polysaccharides and polyfuranoses with the Bio-Rad Laboratories Platelia Aspergillus EIA test have been reported. Therefore, positive test results in patients receiving piperacillin and tazobactam should be interpreted cautiously and confirmed by other diagnostic methods.

As with other penicillins, the administration of ZOSYN may result in a false-positive reaction for glucose in the urine using a copper-reduction method (CLINITEST®). It is recommended that glucose tests based on enzymatic glucose oxidase reactions be used.

8 USE IN SPECIFIC POPULATIONS

8.1 Pregnancy

Risk Summary

Piperacillin and tazobactam cross the placenta in humans. However, there are insufficient data with piperacillin and/or tazobactam in pregnant women to inform a drug-associated risk for major birth defects and miscarriage. No fetal structural abnormalities were observed in rats or mice when piperacillin and tazobactam was administered intravenously during organogenesis at doses 1 to 2 times and 2 to 3 times the human dose of piperacillin and tazobactam, respectively, based on body-surface area (mg/m^2). However, fetotoxicity in the presence of maternal toxicity was observed in developmental toxicity and peri/postnatal studies conducted in rats (intraperitoneal administration prior to mating and throughout gestation or from gestation day 17 through lactation day 21) at doses less than the maximum recommended human daily dose based on body-surface area (mg/m^2) (see Data).

The background risk of major birth defects and miscarriage for the indicated population is unknown. In the U.S. general population, the estimated background risk of major birth defects and miscarriage in clinically recognized pregnancies is 2-4% and 15-20%, respectively.

Data

Animal Data

In embryo-fetal development studies in mice and rats, pregnant animals received intravenous doses of piperacillin and tazobactam up to 3000/750 mg/kg/day during the period of organogenesis. There was no evidence of teratogenicity up to the highest dose evaluated, which is 1 to 2 times and 2 to 3 times the human dose of piperacillin and tazobactam, in mice and rats respectively, based on body-surface area (mg/m^2). Fetal body weights were reduced in rats at maternally toxic doses at or above 500/62.5 mg/kg/day, minimally representing 0.4 times the human dose of both piperacillin and tazobactam based on body-surface area (mg/m^2).

A fertility and general reproduction study in rats using intraperitoneal administration of tazobactam or the combination piperacillin and tazobactam prior to mating and through the end of gestation, reported a decrease in litter size in the presence of maternal toxicity at 640 mg/kg/day tazobactam (4 times the human dose of tazobactam based on body-surface area), and decreased litter size and an increase in fetuses with ossification delays and variations of ribs, concurrent with maternal toxicity at ≥640/160 mg/kg/day piperacillin and tazobactam (0.5 times and 1 times the human dose of piperacillin and tazobactam, respectively, based on body-surface area).

Peri/postnatal development in rats was impaired with reduced pup weights, increased stillbirths, and increased pup mortality concurrent with maternal toxicity after intraperitoneal administration of tazobactam alone at doses ≥320 mg/kg/day (2 times the human dose based on body surface area) or of the combination piperacillin and tazobactam at doses ≥640/160 mg/kg/day (0.5 times and 1 times the human dose of piperacillin and tazobactam, respectively, based on body-surface area) from gestation day 17 through lactation day 21.

8.2 Lactation

Risk Summary

Piperacillin is excreted in human milk; tazobactam concentrations in human milk have not been studied. No information is available on the effects of piperacillin and tazobactam on the breast-fed child or on milk production. The developmental and health benefits of breastfeeding should be considered along with the mother’s clinical need for ZOSYN and any potential adverse effects on the breastfed child from ZOSYN or from the underlying maternal condition.

8.4 Pediatric Use

The safety and effectiveness of ZOSYN for intra-abdominal infections, and nosocomial pneumonia have been established in pediatric patients 2 months of age and older.

Use of ZOSYN in pediatric patients 2 months of age and older with intra-abdominal infections including appendicitis and/or peritonitis is supported by evidence from well-controlled studies and pharmacokinetic studies in adults and in pediatric patients. This includes a prospective, randomized, comparative, open-label clinical trial with 542 pediatric patients 2 to 12 years of age with intra-abdominal infections (including appendicitis and/or peritonitis), in which 273 pediatric patients received piperacillin and tazobactam [see Adverse Reactions (6.1) and Clinical Pharmacology (12.3)].

Use of ZOSYN in pediatric patients 2 months of age and older with nosocomial pneumonia is supported by evidence from well-controlled studies in adults with nosocomial pneumonia, a simulation study performed with a population pharmacokinetic model, and a retrospective, cohort study of pediatric patients with nosocomial pneumonia in which 140 pediatric patients were treated with ZOSYN and 267 patients treated with comparators (which included ticarcillin‑clavulanate, carbapenems, ceftazidime, cefepime, or ciprofloxacin) [see Adverse Reactions (6.1) and Clinical Pharmacology (12.3)].

Because of the limitations of the available strengths and administration requirements (i.e., administration of fractional doses is not recommended) of ZOSYN Injection supplied in GALAXY Containers, and to avoid unintentional overdose, this product is not recommended for use if a dose of ZOSYN Injection in GALAXY Containers that does not equal 2.25 g, 3.375 g, or 4.5 g is required and an alternative formulation of ZOSYN should be considered [see Dosage and Administration (2.1, 2.5, and 2.6)].

The safety and effectiveness of ZOSYN have not been established in pediatric patients less than 2 months of age [see Clinical Pharmacology (12) and Dosage and Administration (2)].

Dosage of ZOSYN in pediatric patients with renal impairment has not been determined.

8.5 Geriatric Use

Patients over 65 years are not at an increased risk of developing adverse effects solely because of age. However, dosage should be adjusted in the presence of renal impairment [see Dosage and Administration (2)].

In general, dose selection for an elderly patient should be cautious, usually starting at the low end of the dosing range, reflecting the greater frequency of decreased hepatic, renal, or cardiac function, and of concomitant disease or other drug therapy.

ZOSYN contains 65 mg (2.84 mEq) of sodium per gram of piperacillin in the combination product. At the usual recommended doses, patients would receive between 780 and 1040 mg/day (34.1 and 45.5 mEq) of sodium. The geriatric population may respond with a blunted natriuresis to salt loading. This may be clinically important with regard to such diseases as congestive heart failure.

This drug is known to be substantially excreted by the kidney, and the risk of toxic reactions to this drug may be greater in patients with impaired renal function. Because elderly patients are more likely to have decreased renal function, care should be taken in dose selection, and it may be useful to monitor renal function.

8.6 Renal Impairment

In patients with creatinine clearance ≤ 40 mL/min and dialysis patients (hemodialysis and CAPD), the intravenous dose of ZOSYN should be reduced to the degree of renal function impairment [see Dosage and Administration (2)].

8.7 Hepatic Impairment

Dosage adjustment of ZOSYN is not warranted in patients with hepatic cirrhosis [see Clinical Pharmacology (12.3)].

8.8 Patients with Cystic Fibrosis

As with other semisynthetic penicillins, piperacillin therapy has been associated with an increased incidence of fever and rash in cystic fibrosis patients.

10 OVERDOSAGE

There have been postmarketing reports of overdose with piperacillin and tazobactam. The majority of those events experienced, including nausea, vomiting, and diarrhea, have also been reported with the usual recommended dosages. Patients may experience neuromuscular excitability or seizures if higher than recommended doses are given intravenously (particularly in the presence of renal failure) [see Warnings and Precautions (5.6)].

Treatment should be supportive and symptomatic according to the patient's clinical presentation. Excessive serum concentrations of either piperacillin or tazobactam may be reduced by hemodialysis. Following a single 3.375 g dose of piperacillin and tazobactam, the percentage of the piperacillin and tazobactam dose removed by hemodialysis was approximately 31% and 39%, respectively [see Clinical Pharmacology (12)].

11 DESCRIPTION

ZOSYN (piperacillin and tazobactam) Injection is an injectable antibacterial combination product consisting of the semisynthetic antibacterial piperacillin sodium and the beta-lactamase inhibitor tazobactam sodium for intravenous administration.

Piperacillin sodium is derived from D(-)-α-aminobenzyl-penicillin. The chemical name of piperacillin sodium is sodium (2S,5R,6R)-6-[(R)-2-(4-ethyl-2,3-dioxo-1-piperazine-carboxamido)-2-phenylacetamido]-3,3-dimethyl-7-oxo-4-thia-1-azabicyclo[3.2.0]heptane-2-carboxylate. The chemical formula is C23H26N5NaO7S and the molecular weight is 539.5. The chemical structure of piperacillin sodium is:

Tazobactam sodium, a derivative of the penicillin nucleus, is a penicillanic acid sulfone. Its chemical name is sodium (2S,3S,5R)-3-methyl-7-oxo-3-(1H-1,2,3-triazol-1-ylmethyl)-4-thia-1-azabicyclo[3.2.0]heptane-2-carboxylate-4,4-dioxide. The chemical formula is C10H11N4NaO5S and the molecular weight is 322.3. The chemical structure of tazobactam sodium is:

ZOSYN Injection in the GALAXY Container is a frozen iso-osmotic sterile non-pyrogenic premixed solution. The components and dosage formulations are given in the table below:

Table 6: ZOSYN In GALAXY Containers Premixed Frozen Solution
Component [Piperacillin and tazobactam are present in the formulation as sodium salts. Dextrose hydrous, sodium citrate dihydrate, and edetate disodium dihydrate amounts are approximate.] | Function | Dosage Formulations
Component [Piperacillin and tazobactam are present in the formulation as sodium salts. Dextrose hydrous, sodium citrate dihydrate, and edetate disodium dihydrate amounts are approximate.] | Function | 2.25 g/50 mL | 3.375 g/50 mL | 4.5 g/100 mL
Piperacillin | active ingredient | 2 g | 3 g | 4 g
Tazobactam | beta‑lactamase inhibitor | 250 mg | 375 mg | 500 mg
Dextrose Hydrous | osmolality adjusting agent | 1 g | 350 mg | 2 g
Sodium Citrate; Dihydrate | buffering agent | 100 mg | 150 mg | 200 mg
Edetate Disodium; Dihydrate | metal chelator | 0.5 mg | 0.75 mg | 1 mg
Water for Injection | solvent | q.s. 50 mL | q.s. 50 mL | q.s. 100 mL

ZOSYN contains a total of 2.84 mEq (65 mg) of sodium (Na^+) per gram of piperacillin in the combination product.

12 CLINICAL PHARMACOLOGY

12.1 Mechanism of Action

ZOSYN is an antibacterial drug [see Microbiology (12.4)].

12.2 Pharmacodynamics

The pharmacodynamic parameter for piperacillin and tazobactam that is most predictive of clinical and microbiological efficacy is time above MIC.

12.3 Pharmacokinetics

The mean and coefficients of variation (CV%) for the pharmacokinetic parameters of piperacillin and tazobactam after multiple intravenous doses are summarized in Table 7.

Table 7: Mean (CV%) Piperacillin and Tazobactam PK Parameters
Piperacillin
Piperacillin and; Tazobactam; Dose [Piperacillin and tazobactam were given in combination, infused over 30 minutes.] | Cmax (mcg/mL) | AUC [Numbers in []parentheses are coefficients of variation [CV%].] (mcg•h/mL) | CL (mL/min) | V; (L) | T1/2; (h) | CLR (mL/min)
2.25 g | 134 | 131 [14] | 257 | 17.4 | 0.79 | --
3.375 g | 242 | 242 [10] | 207 | 15.1 | 0.84 | 140
4.5 g | 298 | 322 [16] | 210 | 15.4 | 0.84 | --
Tazobactam
Piperacillin and; Tazobactam; Dose | Cmax (mcg/mL) | AUC (mcg•h/mL) | CL (mL/min) | V; (L) | T1/2; (h) | CLR (mL/min)
2.25 g | 15 | 16.0 [21] | 258 | 17.0 | 0.77 | --
3.375 g | 24 | 25.0 [8] | 251 | 14.8 | 0.68 | 166
4.5 g | 34 | 39.8 [15] | 206 | 14.7 | 0.82 | --

Cmax: maximum observed concentration, AUC: Area under the curve, CL=clearance, CLR= Renal clearance

V=volume of distribution, T1/2 = elimination half-life

Peak plasma concentrations of piperacillin and tazobactam are attained immediately after completion of an intravenous infusion of ZOSYN. Piperacillin plasma concentrations, following a 30‑minute infusion of ZOSYN, were similar to those attained when equivalent doses of piperacillin were administered alone. Steady-state plasma concentrations of piperacillin and tazobactam were similar to those attained after the first dose due to the short half-lives of piperacillin and tazobactam.

Distribution

Both piperacillin and tazobactam are approximately 30% bound to plasma proteins. The protein binding of either piperacillin or tazobactam is unaffected by the presence of the other compound. Protein binding of the tazobactam metabolite is negligible.

Piperacillin and tazobactam are widely distributed into tissues and body fluids including intestinal mucosa, gallbladder, lung, female reproductive tissues (uterus, ovary, and fallopian tube), interstitial fluid, and bile. Mean tissue concentrations are generally 50% to 100% of those in plasma. Distribution of piperacillin and tazobactam into cerebrospinal fluid is low in subjects with non-inflamed meninges, as with other penicillins (see Table 8).

Table 8: Piperacillin and Tazobactam Concentrations in Selected Tissues and Fluids after Single 4 g/0.5 g 30-min IV Infusion of ZOSYN
Tissue or Fluid | N [Each subject provided a single sample.] | Sampling period [Time from the start of the infusion] (h) | Mean PIP Concentration Range (mg/L) | Tissue:Plasma Range | Tazo Concentration Range (mg/L) | Tazo Tissue:Plasma Range
Skin | 35 | 0.5 – 4.5 | 34.8 – 94.2 | 0.60 – 1.1 | 4.0 – 7.7 | 0.49 – 0.93
Fatty Tissue | 37 | 0.5 – 4.5 | 4.0 – 10.1 | 0.097 – 0.115 | 0.7 – 1.5 | 0.10 – 0.13
Muscle | 36 | 0.5 – 4.5 | 9.4 – 23.3 | 0.29 – 0.18 | 1.4 – 2.7 | 0.18 – 0.30
Proximal Intestinal Mucosa | 7 | 1.5 – 2.5 | 31.4 | 0.55 | 10.3 | 1.15
Distal Intestinal Mucosa | 7 | 1.5 – 2.5 | 31.2 | 0.59 | 14.5 | 2.1
Appendix | 22 | 0.5 – 2.5 | 26.5 – 64.1 | 0.43 – 0.53 | 9.1 – 18.6 | 0.80 – 1.35

Metabolism

Piperacillin is metabolized to a minor microbiologically active desethyl metabolite. Tazobactam is metabolized to a single metabolite that lacks pharmacological and antibacterial activities.

Excretion

Following single or multiple ZOSYN doses to healthy subjects, the plasma half-life of piperacillin and of tazobactam ranged from 0.7 to 1.2 hours and was unaffected by dose or duration of infusion.

Both piperacillin and tazobactam are eliminated via the kidney by glomerular filtration and tubular secretion. Piperacillin is excreted rapidly as unchanged drug with 68% of the administered dose excreted in the urine. Tazobactam and its metabolite are eliminated primarily by renal excretion with 80% of the administered dose excreted as unchanged drug and the remainder as the single metabolite. Piperacillin, tazobactam and desethyl piperacillin are also secreted into the bile.

Specific Populations

Renal Impairment

After the administration of single doses of piperacillin and tazobactam to subjects with renal impairment, the half-life of piperacillin and of tazobactam increases with decreasing creatinine clearance. At creatinine clearance below 20 mL/min, the increase in half-life is twofold for piperacillin and fourfold for tazobactam compared to subjects with normal renal function. Dosage adjustments for ZOSYN are recommended when creatinine clearance is below 40 mL/min in patients receiving the usual recommended daily dose of ZOSYN. See Dosage and Administration (2) for specific recommendations for the treatment of patients with renal‑impairment.

Hemodialysis removes 30% to 40% of a piperacillin and tazobactam dose with an additional 5% of the tazobactam dose removed as the tazobactam metabolite. Peritoneal dialysis removes approximately 6% and 21% of the piperacillin and tazobactam doses, respectively, with up to 16% of the tazobactam dose removed as the tazobactam metabolite. For dosage recommendations for patients undergoing hemodialysis [see Dosage and Administration (2)].

Hepatic Impairment

The half-life of piperacillin and of tazobactam increases by approximately 25% and 18%, respectively, in patients with hepatic cirrhosis compared to healthy subjects. However, this difference does not warrant dosage adjustment of ZOSYN due to hepatic cirrhosis.

Pediatrics

Piperacillin and tazobactam pharmacokinetics were studied in pediatric patients 2 months of age and older. The clearance of both compounds is slower in the younger patients compared to older children and adults.

In a population PK analysis, estimated clearance for 9 month-old to 12 year-old patients was comparable to adults, with a population mean (SE) value of 5.64 (0.34) mL/min/kg. The piperacillin clearance estimate is 80% of this value for pediatric patients 2 - 9 months old. In patients younger than 2 months of age, clearance of piperacillin is slower compared to older children; however, it is not adequately characterized for dosing recommendations. The population mean (SE) for piperacillin volume of distribution is 0.243 (0.011) L/kg and is independent of age.

Geriatrics

The impact of age on the pharmacokinetics of piperacillin and tazobactam was evaluated in healthy male subjects, aged 18 - 35 years (n=6) and aged 65 to 80 years (n=12). Mean half‑life for piperacillin and tazobactam was 32% and 55% higher, respectively, in the elderly compared to the younger subjects. This difference may be due to age-related changes in creatinine clearance.

Race

The effect of race on piperacillin and tazobactam was evaluated in healthy male volunteers. No difference in piperacillin or tazobactam pharmacokinetics was observed between Asian (n=9) and Caucasian (n=9) healthy volunteers who received single 4/0.5 g doses.

Drug Interactions

The potential for pharmacokinetic drug interactions between ZOSYN and aminoglycosides, probenecid, vancomycin, heparin, vecuronium, and methotrexate has been evaluated [see Drug Interactions (7)].

12.4 Microbiology

Mechanism of Action

Piperacillin sodium exerts bactericidal activity by inhibiting septum formation and cell wall synthesis of susceptible bacteria. In vitro, piperacillin is active against a variety of gram‑positive and gram-negative aerobic and anaerobic bacteria. Tazobactam sodium has little clinically relevant in vitro activity against bacteria due to its reduced affinity to penicillin‑binding proteins. It is, however, a beta-lactamase inhibitor of the Molecular class A enzymes, including Richmond-Sykes class III (Bush class 2b & 2b') penicillinases and cephalosporinases. It varies in its ability to inhibit class II and IV (2a & 4) penicillinases. Tazobactam does not induce chromosomally-mediated beta-lactamases at tazobactam concentrations achieved with the recommended dosage regimen.

Antimicrobial Activity

ZOSYN has been shown to be active against most isolates of the following microorganisms, both in vitro and in clinical infections [see Indications and Usage (1)]:

The following in vitro data are available, but their clinical significance is unknown. At least 90 percent of the following bacteria exhibit an in vitro minimum inhibitory concentration (MIC) less than or equal to the susceptible breakpoint for piperacillin and tazobactam against isolates of similar genus or organism group. However, the efficacy of ZOSYN in treating clinical infections caused by these bacteria has not been established in adequate and well-controlled clinical trials.

† These are not beta-lactamase producing bacteria and, therefore, are susceptible to piperacillin alone.

Susceptibility Testing

For specific information regarding susceptibility test interpretive criteria, and associated test methods and quality control standards recognized by FDA for this drug, please see: https://www.fda.gov/STIC.

13 NONCLINICAL TOXICOLOGY

13.1 Carcinogenesis, Mutagenesis, Impairment of Fertility

Carcinogenesis
Long-term carcinogenicity studies in animals have not been conducted with piperacillin and tazobactam, piperacillin, or tazobactam.

Mutagenesis
Piperacillin and tazobactam was negative in microbial mutagenicity assays, the unscheduled DNA synthesis (UDS) test, a mammalian point mutation (Chinese hamster ovary cell HPRT) assay, and a mammalian cell (BALB/c-3T3) transformation assay. In vivo, piperacillin and tazobactam did not induce chromosomal aberrations in rats.

Fertility
Reproduction studies have been performed in rats and have revealed no evidence of impaired fertility when piperacillin and tazobactam is administered intravenously up to a dose of 1280/320 mg/kg piperacillin and tazobactam, which is similar to the maximum recommended human daily dose based on body-surface area (mg/m^2).

15 REFERENCES

1. Jensen J-US, Hein L, Lundgren B, et al. BMJ Open 2012; 2:e000635. doi:10.1136.

16 HOW SUPPLIED/STORAGE AND HANDLING

ZOSYN® (piperacillin and tazobactam) Injection in GALAXY Containers are supplied as a frozen, iso-osmotic, sterile, nonpyrogenic solution in single‑dose plastic containers as follows:

- 2.25 g (piperacillin sodium equivalent to 2 g piperacillin and tazobactam sodium equivalent to 0.25 g tazobactam) in 50 mL. Each container has 5.58 mEq (128 mg) of sodium. Supplied 24/box—NDC 0338-9632-24
- 3.375 g (piperacillin sodium equivalent to 3 g piperacillin and tazobactam sodium equivalent to 0.375 g tazobactam) in 50 mL. Each container has 8.38 mEq (192 mg) of sodium. Supplied 24/box—NDC 0338-9636-24
- 4.5 g (piperacillin sodium equivalent to 4 g piperacillin and tazobactam sodium equivalent to 0.5 g tazobactam) in 100 mL. Each container has 11.17 mEq (256 mg) of sodium. Supplied 12/box—NDC 0338-9638-12

ZOSYN® Injection in GALAXY Containers should be stored at or below -20°C (-4°F) [see Dosage and Administration (2.6)].

Handle frozen product containers with care. Product containers may be fragile in the frozen state.

17 PATIENT COUNSELING INFORMATION

Serious Hypersensitivity Reactions

Advise patients, their families, or caregivers that serious hypersensitivity reactions, including serious allergic cutaneous reactions, could occur with use of ZOSYN that require immediate treatment. Ask them about any previous hypersensitivity reactions to ZOSYN, other beta-lactams (including cephalosporins), or other allergens [see Warnings and Precautions (5.2)].

Hemophagocytic Lymphohistiocytosis

Prior to initiation of treatment with ZOSYN, inform patients that excessive immune activation may occur with ZOSYN and that they should report signs or symptoms such as fever, rash, or lymphadenopathy to a healthcare provider immediately [see Warnings and Precautions (5.3)].

Diarrhea

Advise patients, their families, or caregivers that diarrhea is a common problem caused by antibacterial drugs, including ZOSYN, which usually ends when the drug is discontinued. Sometimes after starting treatment with antibacterial drugs, patients can develop watery and bloody stools (with or without stomach cramps and fever) even as late as two or more months after having taken the last dose of the drug. If this occurs, patients should contact their physician as soon as possible [see Warnings and Precautions (5.9)].

Antibacterial Resistance

Patients should be counseled that antibacterial drugs including ZOSYN should only be used to treat bacterial infections. They do not treat viral infections (e.g., the common cold). When ZOSYN is prescribed to treat a bacterial infection, patients should be told that although it is common to feel better early in the course of therapy, the medication should be taken exactly as directed. Skipping doses or not completing the full course of therapy may (1) decrease the effectiveness of the immediate treatment and (2) increase the likelihood that bacteria will develop resistance and will not be treatable by ZOSYN or other antibacterial drugs in the future.

Pregnancy and Lactation

Patients should be counseled that ZOSYN can cross the placenta in humans and is excreted in human milk [see Use in Specific Populations (8.1, 8.2)].

Baxter Healthcare Corporation

Deerfield, IL 60015 USA

Made in USA

Baxter, Galaxy and Zosyn are trademarks of Baxter International Inc. or its subsidiaries.

Clinitest is a registered trademark of Siemens Healthcare Diagnostics Inc.

07-19-08-744

PACKAGE/LABEL PRINCIPAL DISPLAY PANEL

Container Label

ZOSYN
2.25 g
Piperacillin and Tazobactam
Injection

NDC 0338-9632-01
Single Dose
Container

50 mL
Iso-osmotic

Code 2G3582
Sterile Nonpyrogenic
Rx only

Store at or below -20°C/-4°F. Thaw at room temperature 20° to 25°C (68° to 77°F)
or under refrigeration 2° to 8°C (36° to 46°F). DO NOT FORCE THAW BY IMMERSION
IN WATER BATHS OR BY MICROWAVE IRRADIATION. Thawed solution remains
stable for 14 days under refrigeration or 24 hours at room temperature.
Do not refreeze. Handle frozen product containers with care. Product containers may
be fragile in the frozen state.
Dosage and Use: For intravenous use only. As directed by a physician. See Package Insert.
Cautions: Do not add supplementary medication or additives. Must not be used
in series connections. Check for minute leaks and solution clarity.
Each 50 mL contains: Piperacillin Sodium equivalent to 2 g Piperacillin and
Tazobactam Sodium equivalent to 0.25 g Tazobactam in Water for Injection.
Approximately 1 g Dextrose Hydrous added to adjust osmolality. Approximately
100 mg Sodium Citrate Dihydrate added as a buffer. pH adjusted with sodium
bicarbonate and hydrochloric acid. pH 5.5 - 6.8
Each 50 mL also contains approximately 0.5 mg Edetate Disodium Dihydrate added
as a metal chelator.

Baxter Logo
Manufactured by
Baxter Healthcare Corporation
Deerfield, IL 60015 USA

07-34-00-2323

Barcode
3 03389 63201 6

Container Label

ZOSYN
3.375 g
Piperacillin and Tazobactam
Injection

NDC 0338-9636-01
Single Dose
Container

50 mL
Iso-osmotic

Code 2G3583
Sterile Nonpyrogenic
Rx only

Store at or below -20°C/-4°F. Thaw at room temperature 20° to 25°C (68° to 77°F)
or under refrigeration 2° to 8°C (36° to 46°F). DO NOT FORCE THAW BY IMMERSION
IN WATER BATHS OR BY MICROWAVE IRRADIATION. Thawed solution remains
stable for 14 days under refrigeration or 24 hours at room temperature.
Do not refreeze. Handle frozen product containers with care. Product containers may
be fragile in the frozen state.
Dosage and Use: For intravenous use only. As directed by a physician. See Package Insert.
Cautions: Do not add supplementary medication or additives. Must not be used
in series connections. Check for minute leaks and solution clarity.
Each 50 mL contains: Piperacillin Sodium equivalent to 3 g Piperacillin and
Tazobactam Sodium equivalent to 0.375 g Tazobactam in Water for Injection.
Approximately 350 mg Dextrose Hydrous added to adjust osmolality. Approximately
150 mg Sodium Citrate Dihydrate added as a buffer. pH adjusted with sodium
bicarbonate and hydrochloric acid. pH 5.5 - 6.8
Each 50 mL also contains approximately 0.75 mg Edetate Disodium Dihydrate added
as a metal chelator.

Baxter Logo
Manufactured by
Baxter Healthcare Corporation
Deerfield, IL 60015 USA

07-34-00-2322

Barcode
3 03389 63601 4

Container Label

ZOSYN
4.5 g
Piperacillin and Tazobactam
Injection

NDC 0338-9638-01
Single Dose
Container

100 mL
Iso-osmotic

Code 2G3584
Sterile Nonpyrogenic
Rx only

Store at or below -20°C/-4°F. Thaw at room temperature 20° to 25°C (68° to 77°F)
or under refrigeration 2° to 8°C (36° to 46°F). DO NOT FORCE THAW BY IMMERSION
IN WATER BATHS OR BY MICROWAVE IRRADIATION. Thawed solution remains
stable for 14 days under refrigeration or 24 hours at room temperature.
Do not refreeze. Handle frozen product containers with care. Product containers may
be fragile in the frozen state.
Dosage and Use: For intravenous use only. As directed by a physician. See Package Insert.
Cautions: Do not add supplementary medication or additives. Must not be used
in series connections. Check for minute leaks and solution clarity.
Each 100 mL contains: Piperacillin Sodium equivalent to 4 g Piperacillin and
Tazobactam Sodium equivalent to 0.5 g Tazobactam in Water for Injection.
Approximately 2 g Dextrose Hydrous added to adjust osmolality. Approximately
200 mg Sodium Citrate Dihydrate added as a buffer. pH adjusted with sodium
bicarbonate and hydrochloric acid. pH 5.5 - 6.8
Each 100 mL also contains approximately 1 mg Edetate Disodium Dihydrate added
as a metal chelator.

Baxter Logo
Manufactured by
Baxter Healthcare Corporation
Deerfield, IL 60015 USA

07-34-00-2321

Barcode
3 03389 63801 8

Carton Label

Thaw at room temperature 20° to 25°C (68° to 77°F) or under refrigeration 2° to 8°C (36° to 46°F). DO NOT FORCE THAW BY
IMMERSION IN WATER BATHS OR BY MICROWAVE IRRADIATION. Thawed solution remains stable for 14 days under
refrigeration 2° to 8°C (36° to 46°F) or 24 hours at room temperature 20° to 25°C (68° to 77°F). Do not refreeze.
Handle frozen product containers with care. Product containers may be fragile in the frozen state.

Manufactured by
Baxter Healthcare Corporation
Deerfield, IL 60015 USA

Baxter Logo

GTIN: 20303389632249
07-04-00-1383

ZOSYN
Rx only

Piperacillin and Tazobactam
Injection

2.25 g

Baxter Logo

2 x 12 x 50 mL Single Dose Containers
Contains 2 boxes of 12 of NDC 0338-9632-01
Iso-osmotic
Store at or
below -20°C/-4°F.
Do not refreeze.

NDC 0338-9632-24
Contains 24 of NDC 0338-9632-01
Code 2G3582

* BAR CODE POSITION ONLY
(01) 20303389632249

GALAXY Container

Sterile Nonpyrogenic

Each 50 mL contains: Piperacillin Sodium equivalent to 2 g Piperacillin and Tazobactam Sodium equivalent to 0.25 g Tazobactam
in Water for Injection. Approximately 1 g Dextrose Hydrous added to adjust osmolality. Approximately 100 mg Sodium Citrate
Dihydrate added as a buffer. pH adjusted with sodium bicarbonate and hydrochloric acid. pH 5.5 - 6.8

Each 50 mL also contains approximately 0.5 mg Edetate Disodium Dihydrate added as a metal chelator.

Dosage and Use: For intravenous use only. As directed by a physician. See package insert.

Cautions: Do not add supplementary medications or additives. Must not be used in series connections. Check for minute leaks
by squeezing thawed bag firmly. If leaks are found, discard bag as sterility may be impaired. Do not use unless solution is clear.

Carton Label

Thaw at room temperature 20° to 25°C (68° to 77°F) or under refrigeration 2° to 8°C (36° to 46°F). DO NOT FORCE THAW BY
IMMERSION IN WATER BATHS OR BY MICROWAVE IRRADIATION. Thawed solution remains stable for 14 days under
refrigeration 2° to 8°C (36° to 46°F) or 24 hours at room temperature 20° to 25°C (68° to 77°F). Do not refreeze.
Handle frozen product containers with care. Product containers may be fragile in the frozen state.

Manufactured by
Baxter Healthcare Corporation
Deerfield, IL 60015 USA

Baxter Logo

GTIN: 20303389636247
07-04-00-1382

ZOSYN
Rx only

Piperacillin and Tazobactam
Injection

3.375 g

Baxter Logo

2 x 12 x 50 mL Single Dose Containers
Contains 2 boxes of 12 of NDC 0338-9636-01
Iso-osmotic
Store at or
below -20°C/-4°F.
Do not refreeze.

NDC 0338-9636-24
Contains 24 of NDC 0338-9636-01
Code 2G3583

* BAR CODE POSITION ONLY
(01) 20303389636247

GALAXY Container

Sterile Nonpyrogenic

Each 50 mL contains: Piperacillin Sodium equivalent to 3 g Piperacillin and Tazobactam Sodium equivalent to 0.375 g Tazobactam
in Water for Injection. Approximately 350 mg Dextrose Hydrous added to adjust osmolality. Approximately 150 mg Sodium Citrate
Dihydrate added as a buffer. pH adjusted with sodium bicarbonate and hydrochloric acid. pH 5.5 - 6.8

Each 50 mL also contains approximately 0.75 mg Edetate Disodium Dihydrate added as a metal chelator.

Dosage and Use: For intravenous use only. As directed by a physician. See package insert.

Cautions: Do not add supplementary medications or additives. Must not be used in series connections. Check for minute leaks
by squeezing thawed bag firmly. If leaks are found, discard bag as sterility may be impaired. Do not use unless solution is clear.

Carton Label

Thaw at room temperature 20° to 25°C (68° to 77°F) or under refrigeration 2° to 8°C (36° to 46°F). DO NOT FORCE THAW BY
IMMERSION IN WATER BATHS OR BY MICROWAVE IRRADIATION. Thawed solution remains stable for 14 days under
refrigeration 2° to 8°C (36° to 46°F) or 24 hours at room temperature 20° to 25°C (68° to 77°F). Do not refreeze.
Handle frozen product containers with care. Product containers may be fragile in the frozen state.

Manufactured by
Baxter Healthcare Corporation
Deerfield, IL 60015 USA

Baxter Logo

GTIN: 20303389638128
07-04-00-1381

ZOSYN
Rx only

Piperacillin and Tazobactam
Injection

4.5 g

Baxter Logo

2 x 6 x 100 mL Single Dose Containers
Contains 2 boxes of 6 of NDC 0338-9638-01
Iso-osmotic
Store at or
below -20°C/-4°F.
Do not refreeze.

NDC 0338-9638-12
Contains 12 of NDC 0338-9638-01
Code 2G3584

* BAR CODE POSITION ONLY
(01) 20303389638128

GALAXY Container

Sterile Nonpyrogenic

Each 100 mL contains: Piperacillin Sodium equivalent to 4 g Piperacillin and Tazobactam Sodium equivalent to 0.5 g Tazobactam
in Water for Injection. Approximately 2 g Dextrose Hydrous added to adjust osmolality. Approximately 200 mg Sodium Citrate
Dihydrate added as a buffer. pH adjusted with sodium bicarbonate and hydrochloric acid. pH 5.5 - 6.8

Each 100 mL also contains approximately 1 mg Edetate Disodium Dihydrate added as a metal chelator.

Dosage and Use: For intravenous use only. As directed by a physician. See package insert.

Cautions: Do not add supplementary medications or additives. Must not be used in series connections. Check for minute leaks
by squeezing thawed bag firmly. If leaks are found, discard bag as sterility may be impaired. Do not use unless solution is clear.